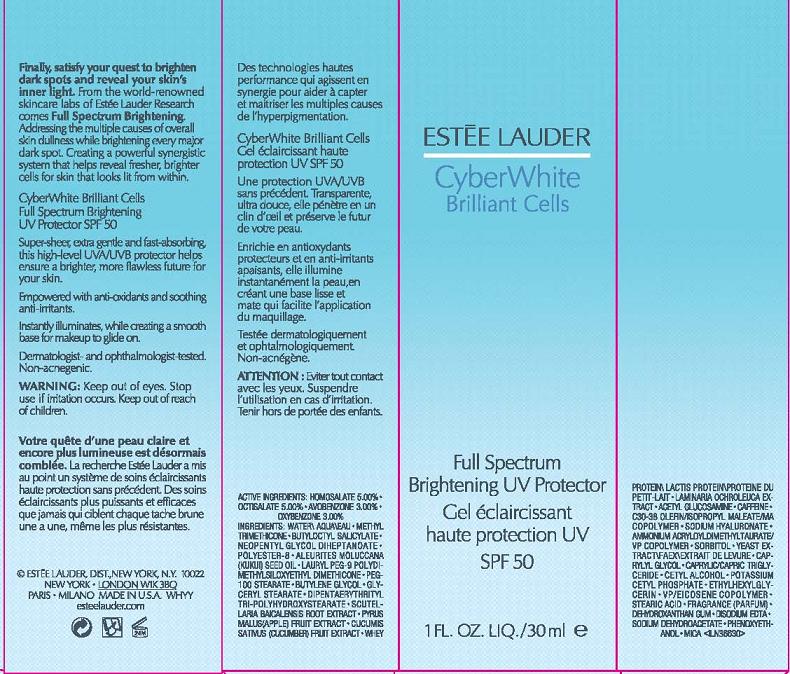 DRUG LABEL: CYBER WHITE
NDC: 11559-006 | Form: LOTION
Manufacturer: ESTEE LAUDER INC
Category: otc | Type: HUMAN OTC DRUG LABEL
Date: 20101108

ACTIVE INGREDIENTS: HOMOSALATE 5.0 mL/100 mL; OCTISALATE 5.0 mL/100 mL; AVOBENZONE 3.0 mL/100 mL; OXYBENZONE 3.0 mL/100 mL
INACTIVE INGREDIENTS: WATER; METHYL TRIMETHICONE; NEOPENTYL GLYCOL DIHEPTANOATE

ACTIVE INGREDIENT

ACTIVE INGREDIENTS: HOMOSALATE 5.00% [] OCTISALATE 5.00% [] AVOBENZONE 3.00% [] OXYBENZONE 3.00%

INACTIVE INGREDIENT

INACTIVE INGREDIENTS: WATER\AQUA\EAU [] METHYL TRIMETHICONE [] BUTYLOCTYL SALICYLATE [] NEOPENTYL GLYCOL DIHEPTANOATE [] POLYESTER-8 [] ALEURITES MOLUCCANA (KUKUI) SEED OIL [] LAURYL PEG-9 POLYDIMETHYLSILOXYETHYL DIMETHICONE [] PEG-100 STEARATE [] BUTYLENE GLYCOL [] GLYCERYL STEARATE [] DIPENTAERYTHRITYL TRI-POLYHYDROXYSTEARATE [] SCUTELLARIA BAICALENSIS ROOT EXTRACT [] PYRUS MALUS (APPLE) FRUIT EXTRACT [] CUCUMIS SATIVUS (CUCUMBER) FRUIT EXTRACT [] WHEY PROTEIN\LACTIS PROTEIN\PROTEINE DU PETIT-LAIT [] LAMINARIA OCHROLEUCA EXTRACT [] ACETYL GLUCOSAMINE [] CAFFEINE [] C30-38 OLEFIN/ISOPROPYL MALEATE/MA COPOLYMER [] SODIUM HYALURONATE [] AMMONIUM ACRYLOYLDIMETHYLTAURATE/VP COPOLYMER [] SORBITOL [] YEAST EXTRACT\FAEX\EXTRAIT DE LEVURE [] CAPRYLYL GLYCOL [] CAPRYLIC/CAPRIC TRIGLYCERIDE [] CETYL ALCOHOL [] POTASSIUM CETYL PHOSPHATE [] ETHYLHEXYLGLYCERIN [] VP/EICOSENE COPOLYMER [] STEARIC ACID [] FRAGRANCE (PARFUM) [] DEHYDROXANTHAN GUM [] DISODIUM EDTA [] SODIUM DEHYDROACETATE [] PHENOXYETHANOL [] MICA

WARNINGS

WARNING: KEEP OUT OF EYES. STOP USE IF IRRITATION OCCURS.

KEEP OUT OF REACH OF CHILDREN

PACKAGE LABEL

CYBER WHITE

BRILLIANT CELLS

FULL SPECTRUM
BRIGHTENING UV PROTECTOR
1 FL OZ LIQ/30 ML
ESTEE LAUDER DISTR.
NEW YORK, NY 10022